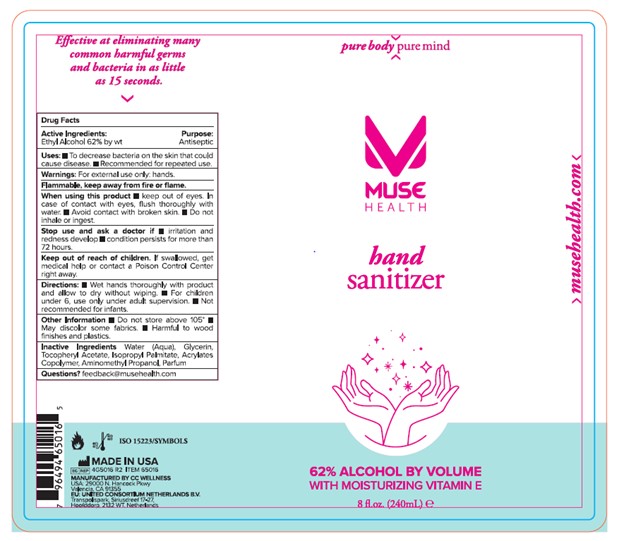 DRUG LABEL: Muse Health Hand Sanitizer
NDC: 71683-011 | Form: GEL
Manufacturer: CC Wellness
Category: otc | Type: HUMAN OTC DRUG LABEL
Date: 20220426

ACTIVE INGREDIENTS: ALCOHOL 62 mL/100 mL
INACTIVE INGREDIENTS: GLYCERIN; WATER; ISOPROPYL PALMITATE; .ALPHA.-TOCOPHEROL ACETATE; ACRYLATES CROSSPOLYMER-6; AMINOMETHYL PROPANEDIOL

ACTIVE INGREDIENT

Ethyl Alocohol 62% by wt.

PURPOSE

Antiseptic

Uses

To decrease bacteria on the skin that could cause disease.

Recommended for repeated use.

WARNINGS

For external use only: hands

When using this product

Keep out of eyes.

In case of contact with eyes, flush thoroughly with water.

Avoid contact with broken skin.

Do not inhale or ingest.

Stop use and ask a doctor

Irritation and redness develop

Condition persists for more than 72 hours

KEEP OUT OF REACH OF CHILDREN

If swallowed, get medical help or contact a Poison Control Center Right Away

Directions

Wet hands thoroughly with product and allow to dry without wiping.

For children under 6, use only under adult supervision.

Not recommended for infants.

Other Information

Do not store above 105°

May discolor some fabrics

Harmful to wood finishes and plastics

INACTIVE INGREDIENT

Water (Aqua), Glycerin, Tocopheryl Acetate, Isopropyl Palmitate, Acrylates Copolymer, Aminomethyl Propranolol, Parfum

Questions?

feedback@musehealth.com